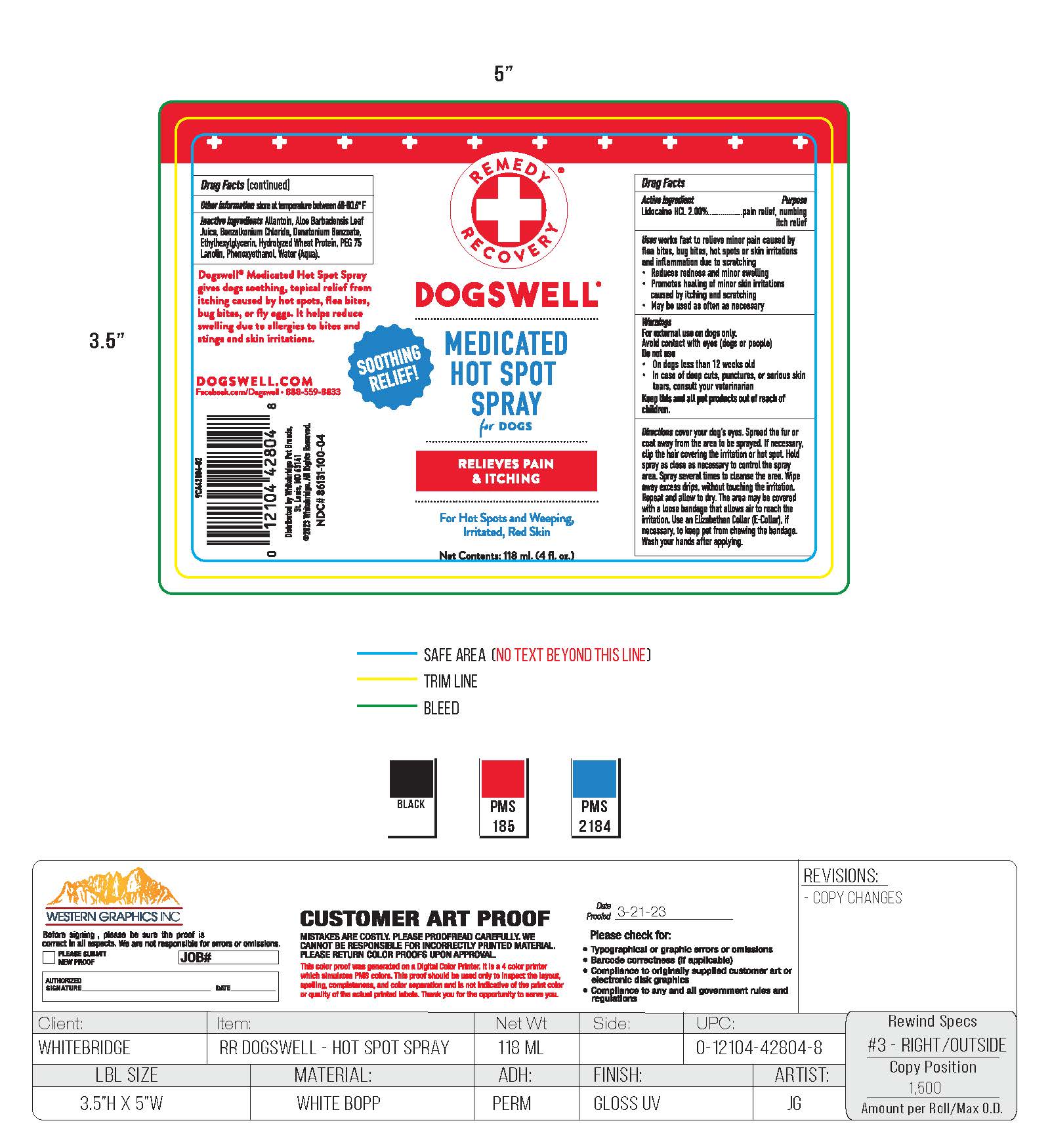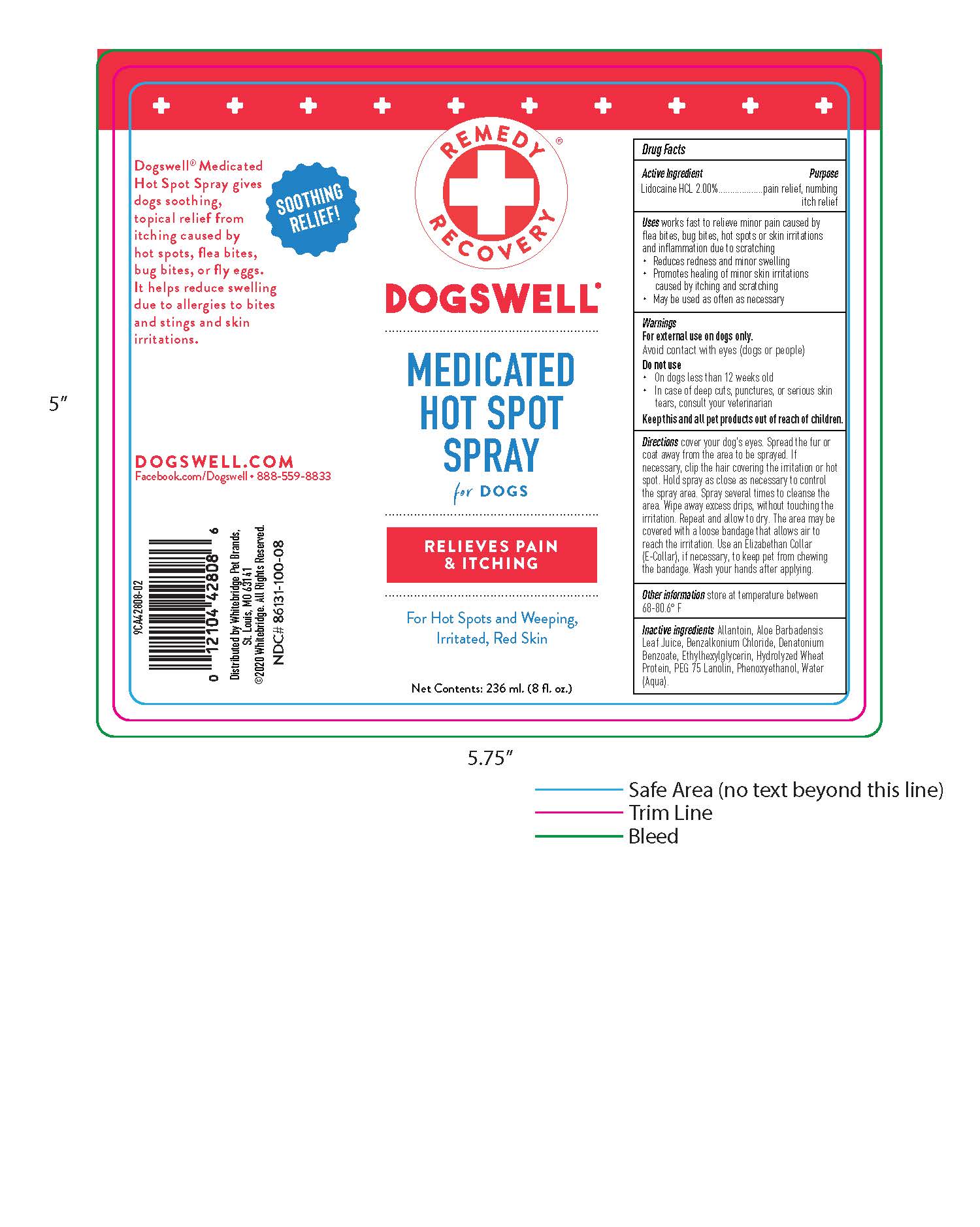 DRUG LABEL: Itch Relief
NDC: 86131-100 | Form: SPRAY
Manufacturer: Whitebridge Pet Brands
Category: animal | Type: OTC ANIMAL DRUG LABEL
Date: 20260107

ACTIVE INGREDIENTS: LIDOCAINE 2.0 g/100 g
INACTIVE INGREDIENTS: WATER; BENZALKONIUM CHLORIDE; ALLANTOIN; ALOE VERA LEAF; PEG-75 LANOLIN; PHENOXYETHANOL; ETHYLHEXYLGLYCERIN; HYDROLYZED WHEAT PROTEIN (ENZYMATIC; 3000 MW); DENATONIUM BENZOATE

Hot Spot Spray

Drug Facts

Active Ingredients

Lidocaine HCL 2.00%

Purpose

pain relief, numbing itch relief

Uses works fast to relieve minor pain caused by flea bites, bug bites, hot spots or skin irritations and inflammation due to scratching

- Reduces redness and minor swelling
- Promotes healing of minor skin irritations caused by itching and scratching
- May be used as often as necessary

Warnings

For external use on dogs only.

Avoid contact with eyes (dogs or people)

Do not use

- On dogs less than 12 weeks old
- In case of deep cuts, punctures, or serious skin tears, consult your veterinarian

Keep this and all pet product out of reach of children.

Directions

cover your dog's eyes. Spread the fur or coat away from the area to be sprayed. If necessary, clip the hair covering the irritation or hot spot. Hold spray as close as necessary to control the spray area. Spray several times to cleanse the area. Wipe away excess drips, without touching the irritation. Repeat and allow to dry. The area may be covered with a loose bandage that allows air to reach the irritation. Use Elizabethan Collar (E-Collar), if necessary, to keep pet from chewing the bandage. Wash your hands after applying.

Other information

store at temperature between 68-80.6 F

INACTIVE INGREDIENT

Allantoin, Aloe Barbadensis Leaf Juice, Benzalkonium Chloride, Denatonium Benzoate, Ethylhexylglycerin, Hydrolyzed Wheat Protein, PEG 75 Lanolin, Phenoxyethanol, Water (Aqua).

Soothing Relief!

Dogswell Medicated Hot Spot Spray givesogs soothing, topical relief from itching caused by hot spots, flea bites, bug bites, or fly eggs. It helps reduce swelling due to allergies to bites and stings and skin irriatations.

DOGSWELL.COM

Facebook.com/Dogswell 888-559-8833

Distrubuted by Whitebridge Pet Brands,

St. Louis, MO 63141

2020 Whitebridge. All Rights Reserved.

NDC#86131-100-08

Remedy Recovery

DOGSWELL

MEDICATED HOT SPOT SPRAY

for DOGS

RELIEVES PAIN & ITCHING

For Hot Spots and Weeping, Irritated, Red Skin

Net Contents: 236 ml. (8 fl. oz.)